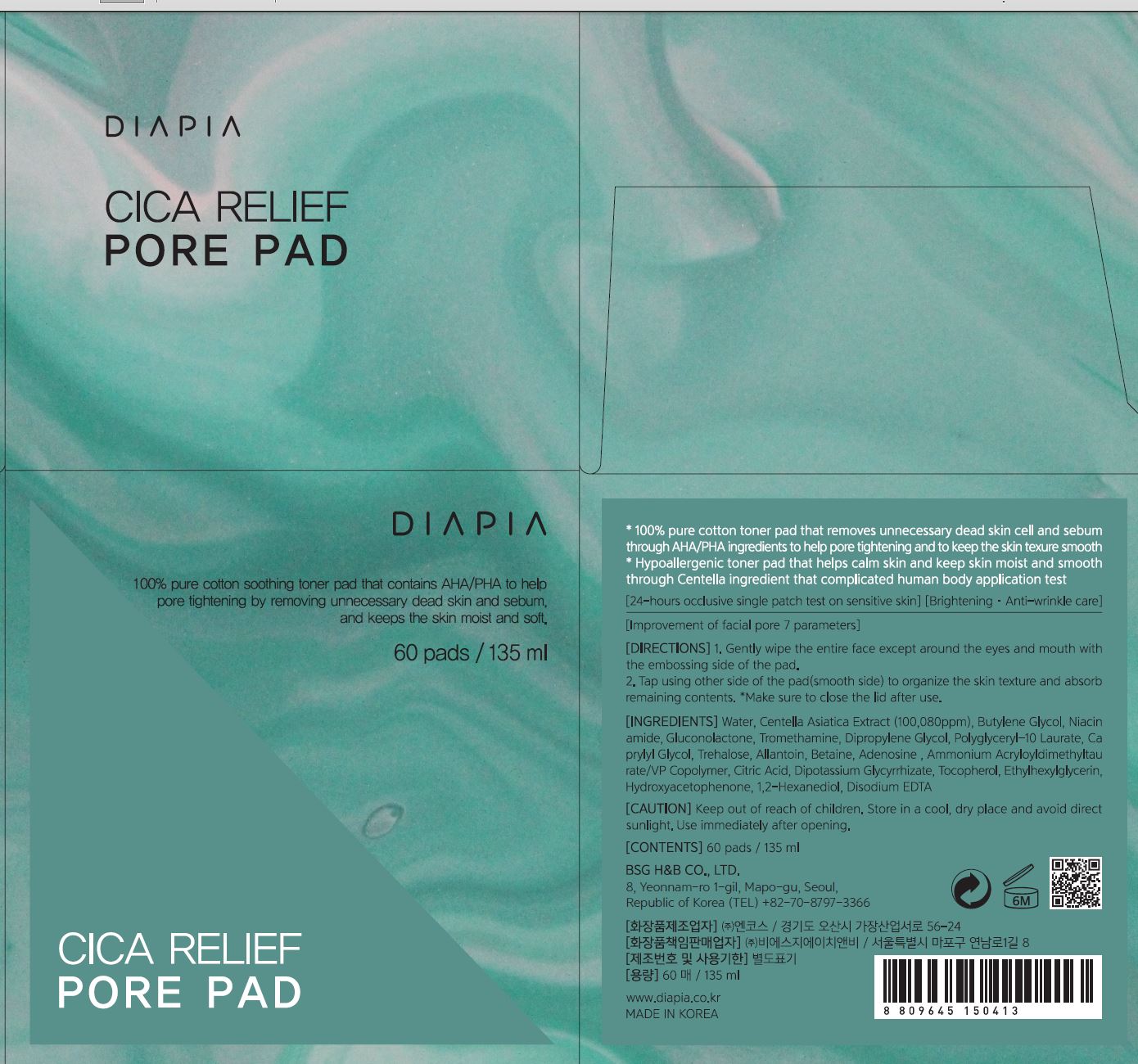 DRUG LABEL: DIAPIA CICA Relief Pore Pad
NDC: 71857-0020 | Form: LIQUID
Manufacturer: BSG H & B Co., Ltd.
Category: otc | Type: HUMAN OTC DRUG LABEL
Date: 20211210

ACTIVE INGREDIENTS: ADENOSINE 0.04 g/100 mL; NIACINAMIDE 2 g/100 mL
INACTIVE INGREDIENTS: WATER

Drug Facts

ACTIVE INGREDIENT

Niacinamide

adenosine

INACTIVE INGREDIENT

Water
Butylene Glycol
Gluconolactone
Tromethamine
Dipropylene Glycol
Hydroxyacetophenone
1,2-Hexanediol
Polyglyceryl-10 Laurate
Caprylyl Glycol
Centella Asiatica Extract
Betaine
Allantoin
Trehalose
Ethylhexylglycerin
Disodium EDTA
Citric Acid
Ammonium Acryloyldimethyltaurate/VP Copolymer
Dipotassium Glycyrrhizate
Tocopherol

PURPOSE

Brightening, anti wrinkle care

keep out of reach of the children

INDICATIONS AND USAGE

gently wipe the entire face except around the eyes and mouth with the embossing side of the pad

tap, using other side of the pad (smooth side) to organize the skin texture and absorb remaining contents

make sure to close the lid after use

WARNINGS

1.Keep out of reach of children.

2.Store in a cool, dry place and avoid direct sunlight.

3.If abnormal symptoms occur after use, stop use and consult with a skin specialist.

DOSAGE AND ADMINISTRATION

for external use only